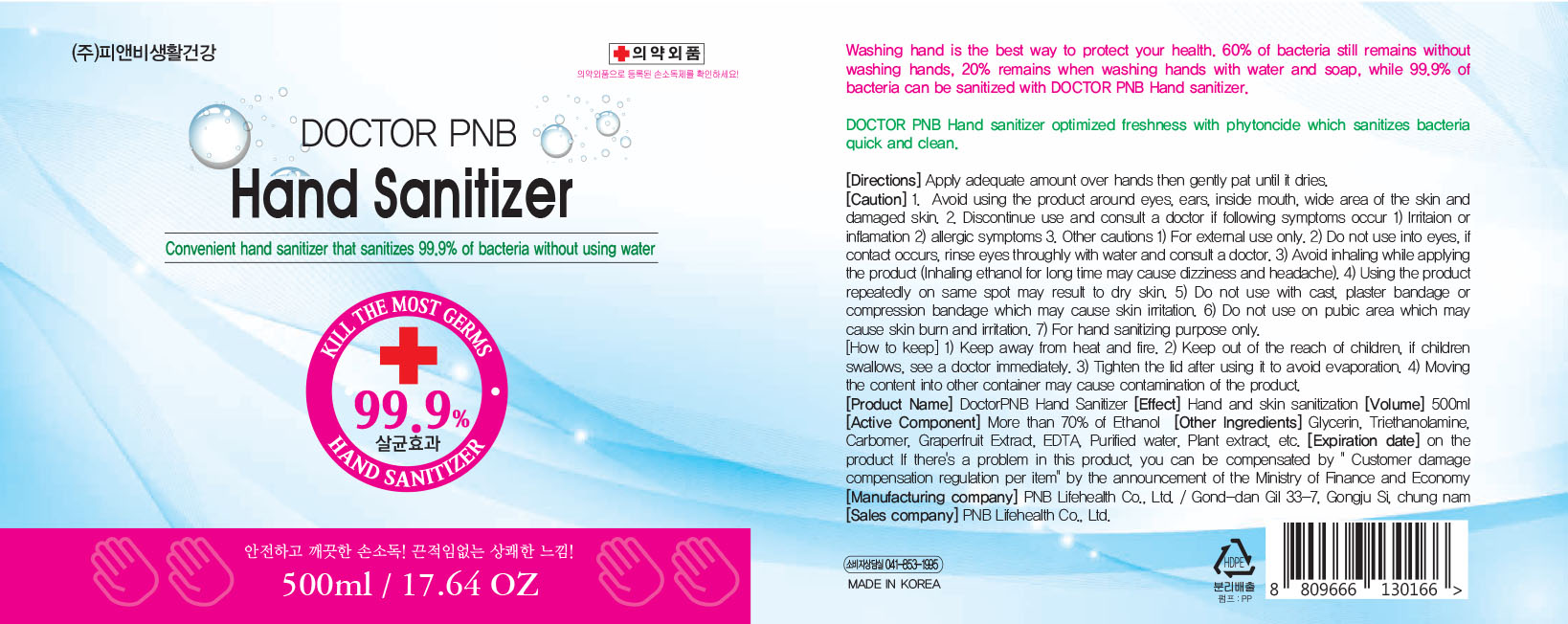 DRUG LABEL: DoctorPNB Hand Sanitizer
NDC: 79544-301 | Form: LIQUID
Manufacturer: PNB LIFEHEALTH co., Ltd.
Category: otc | Type: HUMAN OTC DRUG LABEL
Date: 20211214

ACTIVE INGREDIENTS: ALCOHOL 70 mL/100 mL
INACTIVE INGREDIENTS: WATER 28.55 mL/100 mL; POLYACRYLIC ACID (250000 MW) 0.25 mL/100 mL; TROLAMINE 0.2 mL/100 mL; GLYCERIN 1 mL/100 mL

sanitizer

Active Ingredient

alchol70%

PURPOSE

Antiseptic

inactive ingredient

carbomer, water,triethanolamine, isocyanate polymer, polyacrylic acid

Direction

Apply adequate amount over hands then gently pat until it dry.

Use

Hand sanitizer to help reduce bacteria that potentially can cause disease.
For use when soap and water are not avaliable.

Warnings

Disontinue use amd consult a doctor following symptoms occur irritation or inflamation allergic symptoms.

do not use into eyes, if contact occurs, rinse eyes throughly with water and consult doctor

Keep out of reach of children

If swallowed contact your doctor immediately

Stop use and ask a doctor

if the following symptoms appear,Stop use and immediately consult a doctor: rash, erythema, itching, edema or any other skin irritation.

Other information

keep container upright. Store at room temperature (1-30'C)

keep away from heat and fire

indication

After use, properly close the product to avoid drying out or spilling.

Take an appropriate amount on your hands and rub thoroughly to dry.

79544-301-01